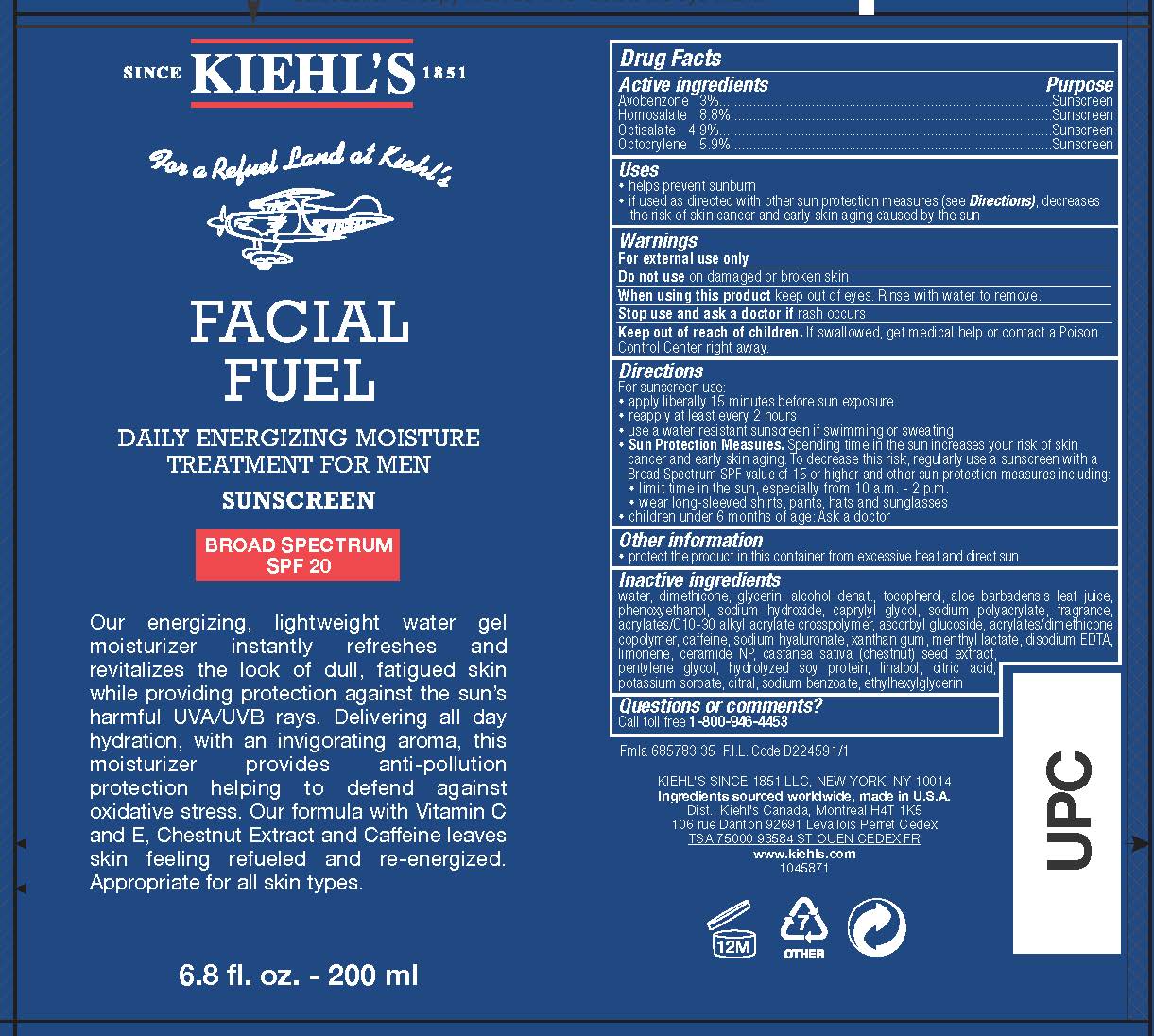 DRUG LABEL: Kiehls Since 1851 Facial Fuel Daily Energizing Moisture Treatment for Men Broad Spectrum SPF 20 Sunscreen
NDC: 49967-608 | Form: LOTION
Manufacturer: L'Oreal USA Products Inc
Category: otc | Type: HUMAN OTC DRUG LABEL
Date: 20231230

ACTIVE INGREDIENTS: Avobenzone 30 mg/1 mL; HOMOSALATE 88 mg/1 mL; Octisalate 49 mg/1 mL; Octocrylene 59 mg/1 mL
INACTIVE INGREDIENTS: WATER; GLYCERIN; DIMETHICONE; ALCOHOL; TOCOPHEROL; ALOE VERA LEAF; PHENOXYETHANOL; SODIUM HYDROXIDE; CAPRYLYL GLYCOL; SODIUM POLYACRYLATE (8000 MW); CARBOMER INTERPOLYMER TYPE A (ALLYL SUCROSE CROSSLINKED); ASCORBYL GLUCOSIDE; CAFFEINE; HYALURONATE SODIUM; XANTHAN GUM; METHYL LACTATE, (-)-; EDETATE DISODIUM; LIMONENE, (+)-; CERAMIDE NP; SPANISH CHESTNUT; PENTYLENE GLYCOL; HYDROLYZED SOY PROTEIN (ENZYMATIC; 2000 MW); LINALOOL, (+/-)-; CITRIC ACID MONOHYDRATE; POTASSIUM SORBATE; CITRAL; SODIUM BENZOATE; ETHYLHEXYLGLYCERIN

Drug Facts

Active ingredients

Avobenzone 3%

Homosalate 8.8%

Octisalate 4.9%

Octocrylene 5.9%

Purpose

Sunscreen

Uses

- helps prevent sunburn

- if used as directed with other sun protection measures (see Directions), decreases the risk of skin cancer and early skin aging caused by the sun

Warnings

For external use only

Do not use

on damaged or broken skin

When using this product

keep out of eyes. Rinse with water to remove.

Stop use and ask a doctor if

rash occurs

Keep out of reach of children.

If swallowed, get medical help or contact a Poison Control Center right away.

Directions

For sunscreen use:

● apply liberally 15 minutes before sun exposure

● reapply at least every 2 hours

● use a water resistant sunscreen if swimming or sweating

● Sun Protection Measures. Spending time in the sun increases your risk of skin cancer and early skin aging. To decrease this risk, regularly use a sunscreen with a Broad Spectrum SPF value of 15 or higher and other sun protection measures including:

● limit time in the sun, especially from 10 a.m. – 2 p.m.

● wear long-sleeved shirts, pants, hats, and sunglasses

● children under 6 months of age: Ask a doctor

Other information

protect the product in this container from excessive heat and direct sun

Inactive ingredients

water, dimethicone, glycerin, alcohol denat., tocopherol, aloe barbadensis leaf juice, phenoxyethanol, sodium hydroxide, caprylyl glycol, sodium polyacrylate, fragrance, acrylates/c10-30 alkyl acrylate crosspolymer, ascorbyl glucoside, acrylates/dimethicone copolymer, caffeine, sodium hyaluronate, xanthan gum, menthyl lactate, disodium EDTA, limonene, ceramide NP, castanea sativa (chestnut) seed extract, pentylene glycol, hydrolyzed soy protein, linalool, citric acid, potassium sorbate, citral, sodium benzoate, ethylhexylglycerin

Questions or comments?

Call toll free 1-800-946-4453